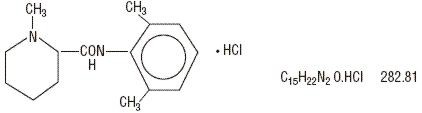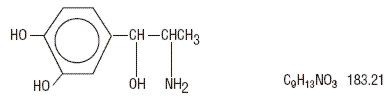 DRUG LABEL: Unknown
Manufacturer: Septodont Inc
Category: prescription | Type: HUMAN PRESCRIPTION DRUG LABELING
Date: 20070330

Isocaine 3% injection
(Mepivacaine Hydrochloride Injection, USP 3%)
Isocaine 2%
with Levonordefrin 1:20,000 injection
(Mepivacaine Hydrochloride and Levonordefrin Injection, USP)

CAUTION: FEDERAL LAW PROHIBITS DISPENSING WITHOUT PRESCRIPTION.

THESE SOLUTIONS ARE INTENDED FOR DENTAL USE ONLY.

DESCRIPTION

ISOCAINE (Mepivacaine Hydrochloride), a tertiary amine used as a local anesthetic, is 1-methyl-2', 6' - pipecoloxylidide monohydrochloride with the following structural formula:

It is a white, crystalline, odorless powder soluble in water, but very resistant to both acid and alkaline hydrolysis.

Levonordefrin, a sympathomimetic amine used as a vasoconstrictor in local anesthetic solution, is (-)-a-(1-Aminoethyl)-3, 4-dihydroxybenzyl alcohol with the following structural formula:

It is a white or buff-colored crystalline solid, freely soluble in aqueous solutions of mineral acids, but practically insoluble in water.

DENTAL CARTRIDGES MAY NOT BE AUTOCLAVED.

ISOCAINE 3% Injection and ISOCAINE 2% with Levonordefrin 1:20,000 Injection are sterile solutions for injection.

COMPOSITION | CARTRIDGE
Each mL contains: | 2% | 3%
Mepivacaine Hydrochloride | 20 mg | 30 mg
Levonordefrin (as the base) | 0.05 mg | -
Sodium Chloride | 4 mg | 3 mg
Sodium Bisulfite | 1 mg | -
Water For Injection, qs. ad. | 1 mL | 1 mL
The pH of the 2% cartridge solution is adjusted between 3.3 and 5.5 with NaOH or HCI.
The pH of the 3% cartridge solution is adjusted between 4.5 and 6.8 with NaOH or HCI.

CLINICAL PHARMACOLOGY

ISOCAINE stabilizes the neuronal membrane and prevents the initiation and transmission of nerve impulses, thereby effecting local anesthesia.

ISOCAINE is rapidly metabolized, with only a small percentage of the anesthetic (5 to 10 percent) being excreted unchanged in the urine. Mepivacaine because of its amide structure, is not detoxified by the circulating plasma esterases. The liver is the principal site of metabolism, with over 50 percent of the administered dose being excreted into the bile as metabolites. Most of the metabolized Mepivacaine is probably resorbed in the intestine and then excreted into the urine since only a small percentage is found in the feces. The principal route of excretion is via the kidney. Most of the anesthetic and its metabolites are eliminated within 30 hours. It has been shown that hydroxylation and N-demethylation, which are detoxification reactions, play important roles in the metabolism of the anesthetic. Three metabolites of Mepivacaine have been identified from adult humans: two phenols, which are excreted almost exclusively as their glucuronide conjugates, and the N-demethylated compound (2', 6' -pipecoloxylidide).

The onset of action is rapid (30 to 120 seconds in the upper jaw; 1 to 4 minutes in the lower jaw) and ISOCAINE 3% without vasoconstrictor will ordinarily provide operating anesthesia of 20 minutes in the upper jaw and 40 minutes in the lower jaw.

ISOCAINE 2% with Levonordefrin 1:20,000 provides anesthesia of longer duration for more prolonged procedures, 1 hour to 2.5 hours in the upper jaw and 2.5 hours to 5.5 hours in the lower jaw.

ISOCAINE does not ordinarily produce irritation or tissue damage.

Levonordefrin is a sympathomimetic amine used as a vasoconstrictor in local anesthetic solutions. It has pharmacologic activity similar to that of Epinephrine but it is more stable than Epinephrine. In equal concentrations, Levonordefrin is less potent than Epinephrine in raising blood pressure, and as a vasoconstrictor.

INDICATIONS AND USAGE

ISOCAINE is indicated for production of local anesthesia for dental procedures by infiltration or nerve block in adults and pediatric patients.

CONTRAINDICATIONS

ISOCAINE is contraindicated in patients with a known hypersensitivity to amide type local anesthetics.

WARNINGS

RESUSCITATIVE EQUIPMENT AND DRUGS SHOULD BE IMMEDIATELY AVAILABLE. (See ADVERSE REACTIONS).

Reactions resulting in fatality have occurred on rare occasions with the use of local anesthetics, even in the absence of a history of hyper- sensitivity.

Fatalities may occur with use of local anesthetics in the head and neck region as the result of retrograde arterial flow to vital CNS areas even when maximum recommended doses are observed. The practitioner should be alert to early evidence of alteration in sensorium or vital signs.

The solution which contains a vasoconstrictor should be used with extreme caution for patients whose medical history and physical evaluation suggest the existence of hypertension, arteriosclerotic heart disease, cerebral vascular insufficiency, heart block, thyrotoxicosis and diabetes, etc.

Isocaine 2% with Levonordefrin 1:20,000 injection (Mepivacaine Hydrochloride and Levonordefrin Injection, USP) contains sodium bisulfite, a sulfite that may cause allergic-type reactions including anaphylactic symptoms and life-threatening or less severe asthmatic episodes in certain susceptible people. The overall prevalence of sulfite sensitivity in the general population is unknown and probably low. Sulfite sensitivity is seen more frequently in asthmatic than in non-asthmatic people. Isocaine 3% injection (Mepivacaine Hydrochloride Injection USP 3%) is SULFITE FREE.

PRECAUTIONS

The safety and effectiveness of Mepivacaine depend upon proper dosage, correct technique, adequate precautions, and readiness for emergencies.

The lowest dose that results in effective anesthesia should be used to avoid high plasma levels and possible adverse effects. Injection of repeated doses of Mepivacaine may cause significant increases in blood levels with each repeated dose due to slow accumulation of the drug or its metabolites, or due to slower metabolic degradation than normal.

Tolerance varies with the status of the patient. Debilitated, elderly patients, acutely ill patients, and pediatric patients should be given reduced doses commensurate with their weight and physical status.

Mepivacaine should be used with caution in patients with a history of severe disturbances of cardiac rhythm or heart block.

INJECTIONS SHOULD ALWAYS BE MADE SLOWLY WITH ASPIRATION TO AVOID INTRAVASCULAR INJECTION AND THEREFORE SYSTEMIC REACTION TO BOTH LOCAL ANESTHETIC AND VASOCONSTRICTOR.

If sedatives are employed to reduce patient apprehension, use reduced doses, since local anesthetic agents, like sedatives, are central nervous system depressants which in combination may have an additive effect. Young pediatric patients should be given minimal doses of each agent.

Changes in sensorium such as excitation, disorientation or drowsiness may be early indications of a high blood level of the drug and may occur following inadvertent intravascular administration or rapid absorption of Mepivacaine.

Local anesthetic procedures should be used with caution when there is inflammation and/or sepsis in the region of the proposed injection.

Information for Patients

The patient should be cautioned against loss of sensation and possibility of biting trauma should the patient attempt to eat or chew gum prior to return of sensation.

Clinically Significant Drug Interactions

The administration of local anesthetic solutions containing vasopressors, such as Levonordefrin, Epinephrine or Norepinephrine, to patients receiving tricyclic antidepressants or monoamine oxidase inhibitors may produce severe, prolonged hypertension. Concurrent use of these agents should generally be avoided. In situations when concurrent therapy is necessary, careful patient monitoring is essential.

Concurrent administration of vasopressor drugs and of ergot-type oxytocic drugs may cause severe, persistent hypertension or cerebrovascular accidents.

Phenothiazines and butyrophenones may reduce or reverse the pressor effect of Epinephrine.

Solutions containing a vasoconstrictor should be used cautiously in the presence of disease which may adversely affect the patient's cardiovascular system. Serious cardiac arrhythmias may occur if preparations containing a vasoconstrictor are employed in patients during or following the administration of potent inhalation anesthetics.

MEPIVACAINE SHOULD BE USED WITH CAUTION IN PATIENTS WITH KNOWN DRUG ALLERGIES AND SENSITIVITIES. A thorough history of the patient's prior experience with Mepivacaine or other local anesthetics as well as concomitant or recent drug use should be taken (see CONTRAINDICATIONS). Patients allergic to methylparaben or para-aminobenzoic acid derivatives (procaine, tetracaine, benzocaine, etc.) have not shown cross-sensitivity to agents of the amide type such as Mepivacaine. Since Mepivacaine is metabolized in the liver and excreted by the kidneys, it should be used cautiously in patients with liver and renal disease.

Carcinogenesis, Mutagenesis, Impairment of Fertility

Studies of Mepivacaine in animals to evaluate the carcinogenic and mutagenic potential or the effect on fertility have not been conducted.

Pregnancy Category C

Animal reproduction studies have not been conducted with this solution. It is also not known whether this solution can cause fetal harm when administered to a pregnant woman or can effect reproductive capacity. This should be given to a pregnant woman only if clearly needed.

Nursing Mothers

It is not known whether this drug is excreted in human milk. Because many drugs are excreted in human milk, caution should be exercised when this solution is administered to a nursing woman.

Pediatric Use

Great care must be exercised in adhering to safe concentrations and dosages for pedodontic administration (see DOSAGE AND ADMINISTRATION).

ADVERSE REACTIONS

Systemic adverse reactions involving the central nervous system and the cardiovascular system usually result from high plasma levels due to excessive dosage, rapid absorption, or inadvertent intravascular injection.

A small number of reactions may result from hypersensitivity, idiosyncrasy or diminished tolerance to normal dosage on the part of the patient.

Reactions involving the central nervous system are characterized by excitation and/or depression. Nervousness, dizziness, blurred vision, or tremors may occur followed by drowsiness, convulsions, unconsciousness, and possible respiratory arrest. Since excitement may be transient or absent, the first manifestations may be drowsiness merging into unconsciousness and respiratory arrest.

Cardiovascular reactions are depressant. They may be the result of direct drug effect or more commonly in dental practice, the result of vasovagal reaction, particularly if the patient is in the sitting position. Failure to recognize premonitory signs such as sweating, feeling of faintness, changes in pulse or sensorium may result in progressive cerebral hypoxia and seizure or serious cardiovascular catastrophe. Management consists of placing the patient in the recumbent position and administration of oxygen. Vasoactive drugs such as Ephedrine or Methoxamine may be administered intravenously.

Allergic reactions are rare and may occur as a result of sensitivity to the local anesthetic and are characterized by cutaneous lesions of delayed onset or urticaria, edema and other manifestations of allergy. The detection of sensitivity by skin testing is of limited value. As with other local anesthetics, anaphylactoid reactions to ISOCAINE have occurred rarely. The reaction may be abrupt and severe and is not usually dose related. Localized puffiness and swelling may occur.

OVERDOSAGE

Treatment of a patient with toxic manifestations consists of assuring and maintaining a patient airway and supporting ventilation (respiration) as required. This usually will be sufficient in the management of most reactions. Should a convulsion persist despite ventilatory therapy, small increments of anticonvulsive agents may be given intravenously, such as benzodiazephine (e.g., diazepam) or ultrashort-acting barbiturates (e.g., thiopental or thiamylal) or short-acting barbiturates (e.g., pentobarbital or secobarbital). Cardiovascular depression may require circulatory assistance with intravenous fluids and/or vasopressor (e.g., Ephedrine) as dictated by the clinical situation. Allergic reactions should be managed by conventional means.

IV and SC LD50's in mice for Mepivacaine Hydrochloride 3% are 33 and 258 mg/kg respectively. The acute IV and SC LD50's in mice for Mepivacaine Hydrochloride 2% with Levonordefrin 1:20,000 are 30 and 184 mg/kg respectively.

DOSAGE AND ADMINISTRATION

As with all local anesthetics, the dose varies and depends upon the area to be anesthetized, the vascularity of the tissues, individual tolerance and the technique of anesthesia. The lowest dose needed to provide effective anesthesia should be administered. For specific techniques and procedures refer to standard dental manuals and textbooks.

For infiltration and block injections in the upper or lower jaw, the average dose of 1 cartridge will usually suffice.

Each cartridge contains 1.8 mL (36 mg of 2% or 54 mg of 3%).

Five cartridges (180 mg of the 2% solution or 270 mg of the 3% solution) are usually adequate to effect anesthesia of the entire oral cavity. Whenever a larger dose seems to be necessary for an extensive procedure, the maximum dose should be calculated according to the patient's weight. A dose of up to 3 mg per pound of body weight may be administered. At any single dental sitting the total dose for all injected sites should not exceed 400 mg in adults.

The maximum pediatric dose should be carefully calculated.

Maximum dose for Pediatric Patient =

Pediatric Patient's Weight (lbs.) × Maximum Recommended Dose
150 for Adults (400 mg.)

The following table, approximating these calculations, may also be used as a guide.

 |  | Maximum Allowable Dosage
 |  | 3% Mepivacaine (Plain) | 2% Mepivacaine 1:20,000 Levonordefrin
 |  | 3 mg/lb 270 mg max.) | 3 mg/lb (180 mg max.)
Weight (lb.) | Mg | Number of Cartridges | Mg | Number of Cartridges
20 | 60 | 1.1 | 60 | 1.6
30 | 90 | 1.7 | 90 | 2.5
40 | 120 | 2.2 | 120 | 3.3
50 | 150 | 2.8 | 150 | 4.2
60 | 180 | 3.3 | 180 | 5.0
80 | 240 | 4.4 | 180 | 5.0
100 | 270 | 5.0 | 180 | 5.0
120 | 270 | 5.0 | 180 | 5.0

Adapted from Malamed, Stanley F: Handbook of medical emergencies in the dental office, ed. 2, St. Louis, 1982. The C.V. Mosby Co.

When using ISOCAINE for infiltration or regional block anesthesia, injection should always be made slowly and with frequent aspiration.

Any unused portion of a cartridge should be discarded.

Parenteral drug products should be inspected visually for particulate matter and discoloration prior to administration, whenever solution and container permit.

DISINFECTION OF CARTRIDGES

As in the case of any cartridge, the diaphragm should be disinfected before needle puncture. The diaphragm should be thoroughly swabbed with either pure 91% isopropyl alcohol or 70% ethyl alcohol, USP, just prior to use. Many commercially available alcohol solutions contain ingredients which are injurious to container components and therefore should not be used. Cartridges should not be immersed in any solution.

HOW SUPPLIED

Isocaine 3% Injection; (Mepivacaine Hydrocholoride Injection USP 3%) 1.8 mL dental cartridges, 50 per carton. Isocaine 2% with Levonordefrin 1:20,000 injection; (Mepivacaine Hydrochloride and Levonordefrin Injection; USP) 1.8 mL dental cartridges, 50 per carton.

Both solutions should be stored at controlled room temperature, between 15°C and 30°C (59°F and 86°F). Protect from light. The 2% solution should not be used if its color is pinkish or darker than slightly yellow or it contains a precipitate.

Manufactured by
Novocol Pharmaceutical of Canada Inc.
Cambridge, Ontario N1R 6X3

Rev. #2102/2/97